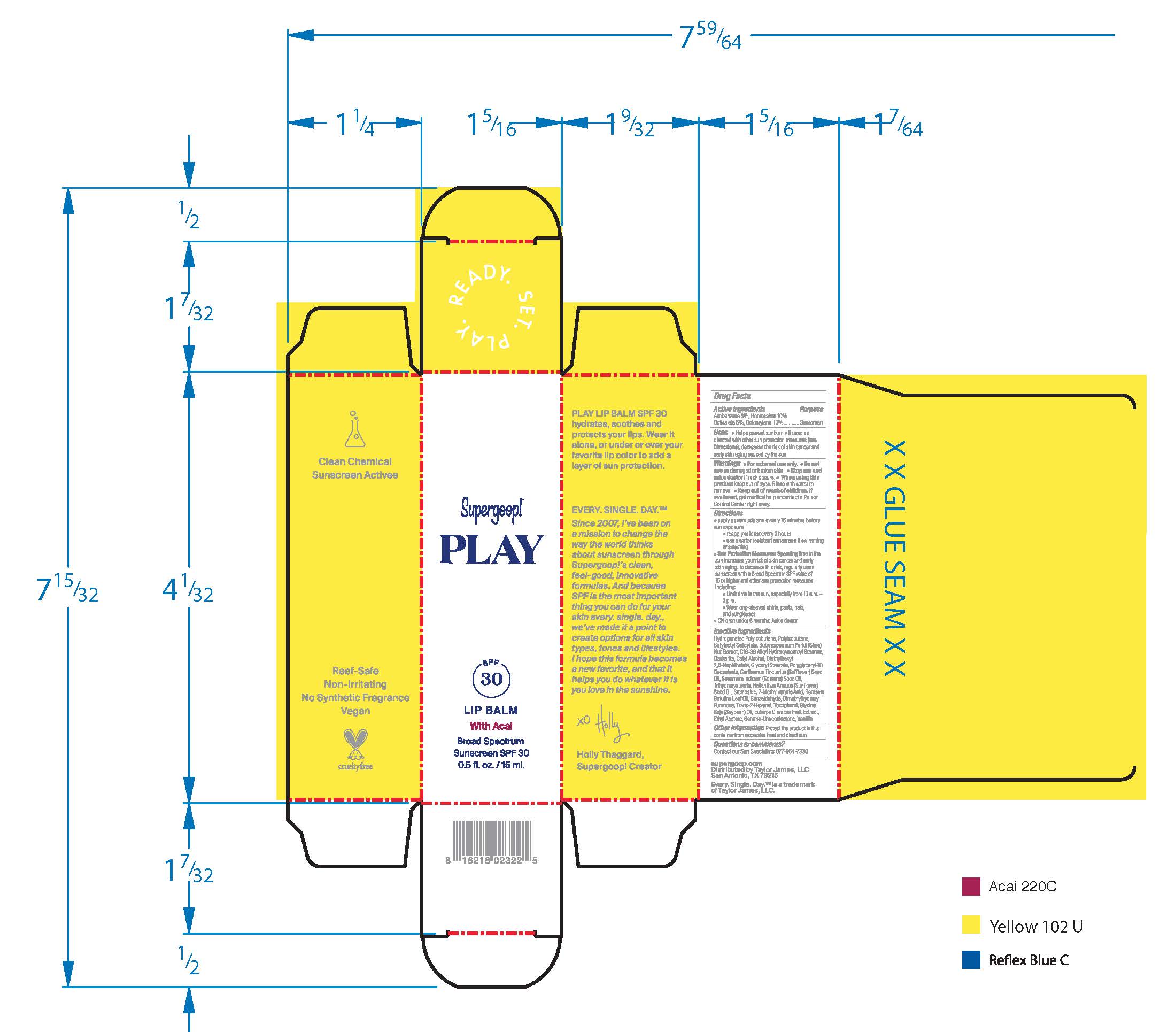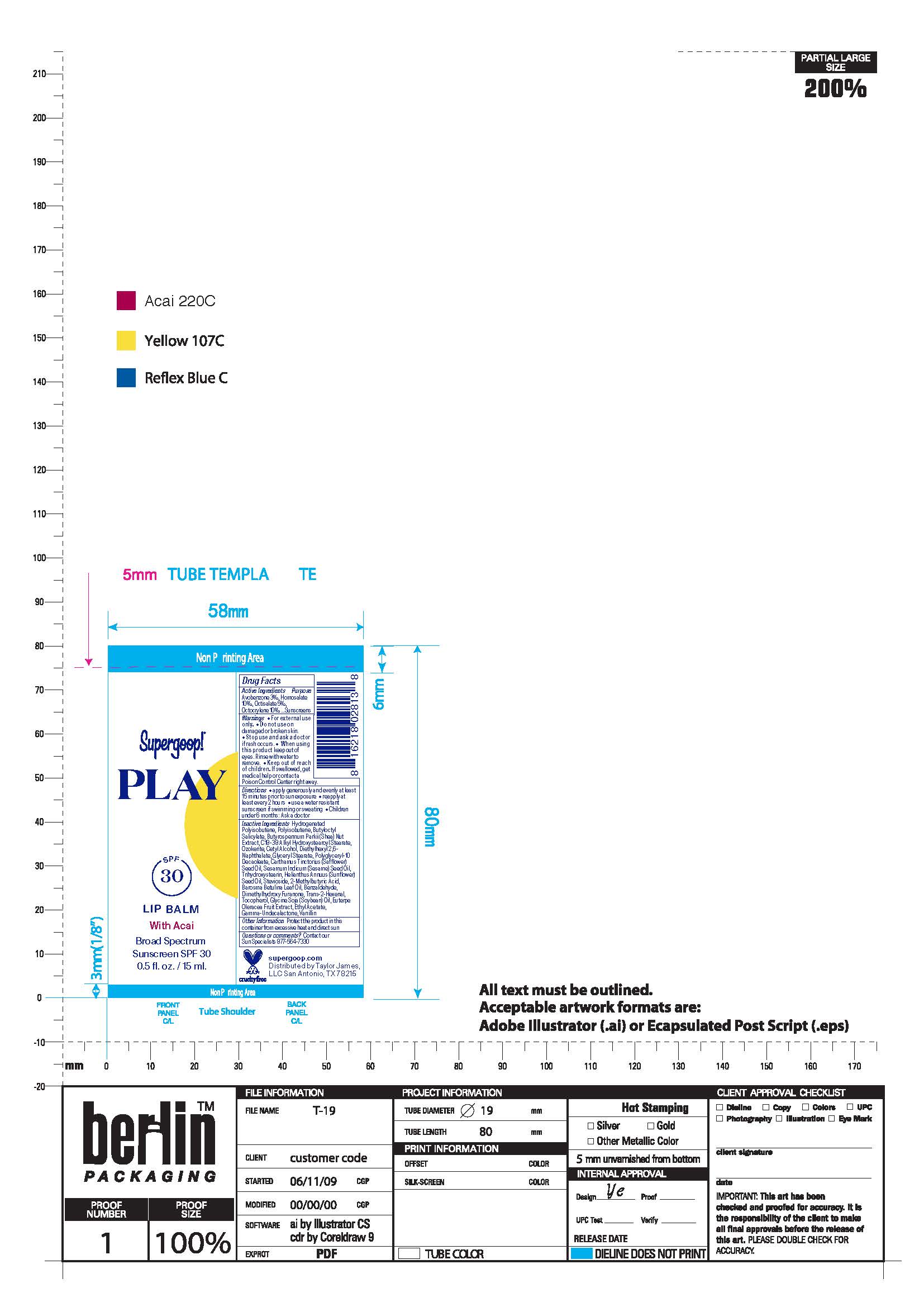 DRUG LABEL: Acaifusion Lip Balm Broad Spectrum SPF 30
NDC: 75936-118 | Form: OINTMENT
Manufacturer: SUPERGOOP LLC
Category: otc | Type: HUMAN OTC DRUG LABEL
Date: 20220325

ACTIVE INGREDIENTS: AVOBENZONE 0.44 g/15 mL; OCTINOXATE 1.11 g/15 mL; OCTISALATE 0.74 g/15 mL
INACTIVE INGREDIENTS: ASCORBYL PALMITATE; SUNFLOWER OIL; ALOE VERA LEAF; CASTOR OIL; D&C RED NO. 27; COCONUT; PETROLATUM; CERESIN; YELLOW WAX; POLYESTER-7; NEOPENTYL GLYCOL DIHEPTANOATE; SORBITAN MONOOLEATE; CANDELILLA WAX; CARNAUBA WAX; POLYSILICONE-15; SOYBEAN OIL; TOCOPHEROL; SHEA BUTTER; HONEY

Acaifusion Lip Balm Broad Spectrum SPF 30

Active Ingredients Purpose

Avobezone 3%, Octinoxate 7.5%, Octisalate 5% Sunscreen

Uses

-Helps prevent and temporarily chafed,chapped, cracked, or windburned skin and/or lips.
-helps prevent sunburn
-If used as directed with other sun protection measures (see Directions),
decreases the risk of skin cancer and early skin aging caused by the sun

· Keep out of reach of children. If product is swallowed, get medical help or
contact a Poison Control Center right away.

· Stop use and ask a doctor if rash occurs

Warnings
· For external use only
· Do not use on damaged or broken skin
· When using this product keep out of eyes. Rinse with water to remove.

Directions

- Apply liberally 15 minutes before sun exposure
- Reapply Liberally as often as necessary.
- Sun Protection Measures. Spending time in the sun increases your risk of skin
cancer and early skin aging. To decrease this risk, regularly use a sunscreen
with broad spectrum SPF of 15 or higher and other sun protection measures
including:
- limit time in the sun, especially from 10 a.m. - 2 p.m.
- wear long-sleeve shirts, pants, hats, and sunglasses
- Reapply at least every 2 hours
- Use a water resistant sunscreen if swimming or sweating

INACTIVE INGREDIENT

Inactive Ingredients-Petrolatum, Ozokerite, Beeswax, Polyester-7, Neopentyl Glycol Diheptanoate, Flavor, Sorbitan Oleate, Euphorbia Cerifera (Candelilla) Wax, Polysilicone-15, Glycine Soja (Soybean) Oil, Tocopherol, Butyrospermum Parkii (Shea) Butter, Honey, Ascorbyl Palmitate, Helianthus Annuus (Sunflower) Seed Oil, Aloe Barbadensis Leaf Extract, Ricinus Communis (Castor) Seed Oil, Red 27 Lake, Cocos Nucifera (Coconut) Fruit Extract

PACKAGE LABEL

Play Lip Balm SPF 30 with Acai